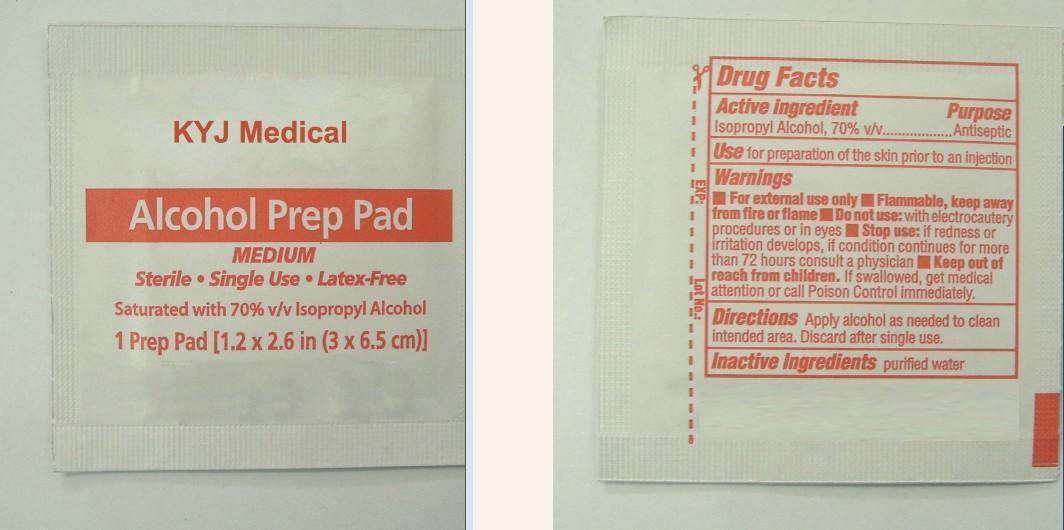 DRUG LABEL: Alcohol Prep
NDC: 76161-001 | Form: SWAB
Manufacturer: KYJ Medical Products Co.,Ltd.
Category: otc | Type: HUMAN OTC DRUG LABEL
Date: 20141010

ACTIVE INGREDIENTS: ISOPROPYL ALCOHOL 0.7 mL/1 1
INACTIVE INGREDIENTS: WATER 0.3 mL/1 1

KYJ Medical Alcohol Prep Pad MEDIUM Sterile ,Single Use, Latex-Free Saturated with 70% v/v Isopropyl Alcohol

Active Ingredient

Isopropyl Alcohol 70%

Purpose

Antiseptic

Use

Use for preparation of the skin prior to an injection

Warnning

For External use only.

Flammable,keep away from fire or flame.

Do not use with electrocautery procedures in eyes.

Stop use and ask a doctor if irritation and redness develop,condition persists for more than 72 hours .

Keep out of reach of children in case of accidental ingestion,seek professional assistance or consult a Poison Control Center immediately.

Directions

Apply alcohol as needed to clean intended area. Discard after single use.

Inactive Ingredients

Inactive Ingredients: Purified Water

Keep out of reach of children in case of accidental ingestion,seek professional assistance or consult a Poison Control Center immediately.